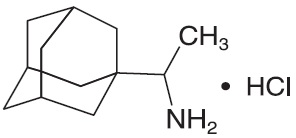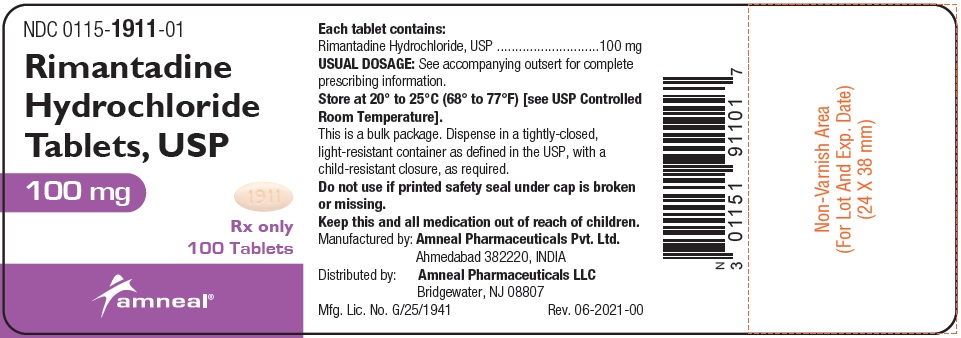 DRUG LABEL: Rimantadine Hydrochloride
NDC: 0115-1911 | Form: TABLET, FILM COATED
Manufacturer: Amneal Pharmaceuticals of New York LLC
Category: prescription | Type: HUMAN PRESCRIPTION DRUG LABEL
Date: 20231231

ACTIVE INGREDIENTS: RIMANTADINE HYDROCHLORIDE 100 mg/1 1
INACTIVE INGREDIENTS: HYPROMELLOSES; MAGNESIUM STEARATE; CELLULOSE, MICROCRYSTALLINE; SODIUM STARCH GLYCOLATE TYPE A POTATO; FD&C YELLOW NO. 6; POLYETHYLENE GLYCOL, UNSPECIFIED

Rimantadine Hydrochloride Tablets, USP
(100 mg)
Rx Only

DESCRIPTION

Rimantadine hydrochloride, USP is a synthetic antiviral drug available as a 100 mg film-coated tablet. Each film-coated tablet contains 100 mg of rimantadine hydrochloride, USP. In addition, each tablet contains the following inactive ingredients: hypromellose, magnesium stearate, microcrystalline cellulose, sodium starch glycolate, type A and FD&C Yellow No. 6 Aluminium Lake. Film coating material, Opadry (YS-1-19025-A), contains hypromellose and polyethylene glycol.

Rimantadine hydrochloride, USP is a white to off-white crystalline powder which is freely soluble in water (50 mg/mL at 20°C).

Chemically, rimantadine hydrochloride, USP is tricyclo [3.3.1.1^3.7]-decane-1-methanamine, α-methyl-, hydrochloride, with a molecular formula of C12H21N•HCl, a molecular weight of 215.77 and the following structural formula:

CLINICAL PHARMACOLOGY

Mechanism of Action

The mechanism of action of rimantadine is not fully understood. Rimantadine appears to exert its inhibitory effect early in the viral replicative cycle, possibly inhibiting the uncoating of the virus. Genetic studies suggest that a virus protein specified by the virion M2 gene plays an important role in the susceptibility of influenza A virus to inhibition by rimantadine.

Microbiology

Rimantadine inhibits the replication in cell culture of influenza A virus isolates from each of the three antigenic subtypes, i.e., H1N1, H2N2 and H3N2, that have been isolated from man. Rimantadine has little or no activity against influenza B virus (Ref. 1, 2). Rimantadine does not appear to interfere with the immunogenicity of inactivated influenza A vaccine.

A quantitative relationship between the susceptibility in cell culture of influenza A virus to rimantadine and clinical response to therapy has not been established.

Susceptibility test results, expressed as the concentration of the drug required to inhibit virus replication by 50% or more in a cell culture system, vary greatly (from 19 nM to 93 µM) depending upon the assay protocol used, size of the virus inoculum, isolates of the influenza A virus strains tested, and the cell types used (Ref. 2).

Resistance

Influenza A virus isolates resistant to rimantadine have been selected in cell culture and in vivo as a result of treatment. Rimantadine-resistant strains of influenza A virus have emerged among freshly isolated strains in closed settings where rimantadine has been used. Resistant viruses have been shown to be transmissible and to cause typical influenza illness (Ref. 3, 9). Substitutions at any one of five amino acid positions in the transmembrane domain of M2 confer resistance to rimantadine. The most common substitution causing resistance among influenza A (H1N1) and A (H3N2) is S31N. Other less common substitutions that cause resistance include substitutions A30F, V27A, V30A, and L26F.

Rimantadine resistance has been observed in circulating seasonal influenza and pandemic isolates from individuals who have not received rimantadine. Swine-origin influenza A (H1N1) (S-OIV) viruses that were resistant to rimantadine have been shown to contain the S31N substitution. Existing primers used for detection of adamantine resistance in seasonal viruses do not work with all tested S-OIVs (Ref. 11). The CDC should be consulted for questions regarding resistance to rimantadine in circulating influenza strains.

Cross-Resistance

Cross-resistance among the adamantanes, rimantadine and amantadine, has been observed. Resistance to rimantadine confers cross-resistance to amantadine and vice-versa. Substitutions that confer resistance to rimantadine include (most frequently) M2 S31N, as well as the less common changes V27A, V30A, L26F and A30T (Ref. 10).

Pharmacokinetics

Although the pharmacokinetic profile of rimantadine hydrochloride has been described, no pharmacodynamic data establishing a correlation between plasma concentration and its antiviral effect are available.

Rimantadine hydrochloride is absorbed after oral administration. The mean ± SD peak plasma concentration after a single 100 mg dose of rimantadine hydrochloride was 74 ± 22 ng/mL (range: 45 to 138 ng/mL). The time to peak concentration was 6 ± 1 hours in healthy adults (age 20 to 44 years). The single dose elimination half-life in this population was 25.4 ± 6.3 hours (range: 13 to 65 hours). The single dose elimination half-life in a group of healthy 71 to 79 year-old subjects was 32 ± 16 hours (range: 20 to 65 hours).

After the administration of rimantadine 100 mg twice daily to healthy volunteers (age 18 to 70 years) for 10 days, area under the curve (AUC) values were approximately 30% greater than predicted from a single dose. Plasma trough levels at steady state ranged between 118 and 468 ng/mL. In these patients no age-related differences in pharmacokinetics were detected. However, in a comparison of three groups of healthy older subjects (age 50 to 60, 61 to 70 and 71 to 79 years), the 71 to 79 year-old group had average AUC values, peak concentrations and elimination half-life values at steady state that were 20 to 30% higher than the other two groups. Steady-state concentrations in elderly nursing home patients (age 68 to 102 years) were 2- to 4-fold higher than those seen in healthy young and elderly adults.

The pharmacokinetic profile of rimantadine in children has not been established.

Following oral administration, rimantadine is extensively metabolized in the liver with less than 25% of the dose excreted in the urine as unchanged drug. Three hydroxylated metabolites have been found in plasma. These metabolites, an additional conjugated metabolite and parent drug account for 74 ± 10% (n=4) of a single 200 mg dose of rimantadine excreted in urine over 72 hours.

In a group (n=14) of patients with chronic liver disease, the majority of whom were stabilized cirrhotics, the pharmacokinetics of rimantadine were not appreciably altered following a single 200 mg oral dose compared to six healthy subjects who were sex, age and weight matched to six of the patients with liver disease. After administration of a single 200 mg dose to patients (n=10) with severe hepatic dysfunction, AUC was approximately 3-fold larger, elimination half-life was approximately 2-fold longer and apparent clearance was about 50% lower when compared to historic data from healthy subjects.

Rimantadine pharmacokinetics were evaluated following administration of 100 mg rimantadine hydrochloride twice daily for 14 days to subjects with mild (creatinine clearance [CrCl] 50 mL/min to 80 mL/min), moderate ([CrCl] 30 mL/min to 49 mL/min), and severe ([CrCl] 5 mL/min to 29 mL/min) renal impairment and to healthy subjects (CrCl > 80 mL/min). There were no clinically relevant differences in rimantadine Cmax, Cmin, and AUC0-τ between subjects with mild or moderate renal impairment compared to healthy subjects. In subjects with severe renal impairment, rimantadine Cmax, Cmin, and AUC0-τ on Day 14 increased by 75%, 82%, and 81%, respectively, compared to healthy subjects. The rimantadine elimination half-life was slightly prolonged (increase of 18% or less) in subjects with mild and moderate renal impairment but increased by 49% in subjects with severe renal impairment compared to healthy subjects.

After a single 200 mg oral dose of rimantadine was given to eight hemodialysis patients (CrCl 0 mL/min to 10 mL/min), there was a 1.6-fold increase in the elimination half-life and a 40% decrease in apparent clearance compared to age-matched healthy subjects. Hemodialysis did not contribute to the clearance of rimantadine.

The in vitro human plasma protein binding of rimantadine is about 40% over typical plasma concentrations. Albumin is the major binding protein.

INDICATIONS AND USAGE

Rimantadine hydrochloride tablet is indicated for the prophylaxis and treatment of illness caused by various strains of influenza A virus in adults (17 years and older).

Rimantadine hydrochloride tablet is indicated for prophylaxis against influenza A virus in children (1 year to 16 years of age).

Prophylaxis

In controlled studies of children (1 year to 16 years of age), healthy adults (17 years and older), and elderly patients (65 years of age and older), rimantadine hydrochloride has been shown to be safe and effective in preventing signs and symptoms of infection caused by various strains of influenza A virus. Since rimantadine hydrochloride does not completely prevent the host immune response to influenza A infection, individuals who take this drug may still develop immune responses to natural disease or vaccination and may be protected when later exposed to antigenically-related viruses. Following vaccination during an influenza outbreak, rimantadine hydrochloride prophylaxis should be considered for the 2 to 4 week time period required to develop an antibody response. However, the safety and effectiveness of rimantadine hydrochloride prophylaxis have not been demonstrated for longer than 6 weeks.

Treatment

Rimantadine hydrochloride therapy should be considered for adults (17 years and older) who develop an influenza-like illness during known or suspected influenza A infection in the community. When administered within 48 hours after onset of signs and symptoms of infection caused by influenza A virus strains, rimantadine hydrochloride has been shown to reduce the duration of fever and systemic symptoms.

The following points should be considered before initiating treatment or prophylaxis with rimantadine hydrochloride:

- Rimantadine hydrochloride is not a substitute for early vaccination on an annual basis as recommended by the Centers for Disease Control and Prevention Advisory Committee on Immunization Practices.
- Influenza viruses change over time. Emergence of resistance mutations could decrease drug effectiveness. Other factors (for example, changes in viral virulence) might also diminish clinical benefit of antiviral drugs. Prescribers should consider available information on influenza drug susceptibility patterns and treatment effects when deciding whether to use rimantadine hydrochloride.

CONTRAINDICATIONS

Rimantadine hydrochloride tablet is contraindicated in patients with known hypersensitivity to drugs of the adamantane class, including rimantadine and amantadine.

PRECAUTIONS

General

An increased incidence of seizures has been reported in patients with a history of epilepsy who received the related drug amantadine. In clinical trials of rimantadine hydrochloride, the occurrence of seizure-like activity was observed in a small number of patients with a history of seizures who were not receiving anticonvulsant medication while taking rimantadine hydrochloride. If seizures develop, rimantadine hydrochloride should be discontinued.

The safety and pharmacokinetics of rimantadine in hepatic insufficiency have only been evaluated after single dose administration. In a study of 14 subjects with chronic liver disease (mostly stabilized cirrhotics), no alterations in the pharmacokinetics were observed after the administration of a single dose of rimantadine. However, the apparent clearance of rimantadine following a single dose to 10 patients with severe liver dysfunction was 50% lower than reported for healthy subjects. Because of the potential for accumulation of rimantadine and its metabolites in plasma, caution should be exercised when patients with hepatic insufficiency are treated with rimantadine.

Following multiple-dose administration of rimantadine, there were no clinically relevant differences in rimantadine systemic exposure between subjects with mild or moderate renal impairment compared to healthy subjects. In subjects with severe renal impairment, rimantadine systemic exposure increased by 81%, compared with healthy subjects. Because of the potential for increased accumulation of rimantadine metabolites in renally impaired subjects, caution should be exercised when these patients are treated with rimantadine.

Transmission of rimantadine resistant virus should be considered when treating patients whose contacts are at high risk for influenza A illness. Influenza A virus strains resistant to rimantadine can emerge during treatment and such resistant strains have been shown to be transmissible and to cause typical influenza illness (Ref. 3). Although the frequency, rapidity, and clinical significance of the emergence of drug-resistant virus are not yet established, several small studies have demonstrated that 10% to 30% of patients with initially sensitive virus, upon treatment with rimantadine, shed rimantadine resistant virus. (Ref. 3, 4, 5, 6)

Clinical response to rimantadine, although slower in those patients who subsequently shed resistant virus, was not significantly different from those who did not shed resistant virus. (Ref. 3) No data are available in humans that address the activity or effectiveness of rimantadine therapy in subjects infected with resistant virus.

Serious bacterial infections may begin with influenza-like symptoms or may coexist with or occur as complications during the course of influenza. Rimantadine hydrochloride has not been shown to prevent such complications.

Drug Interactions

Acetaminophen: Rimantadine hydrochloride, 100 mg, was given twice daily for 13 days to 12 healthy volunteers. On day 11, acetaminophen (650 mg four times daily) was started and continued for 8 days. The pharmacokinetics of rimantadine were assessed on days 11 and 13. Co-administration with acetaminophen reduced the peak concentration and AUC values for rimantadine by approximately 11%.

Aspirin: Rimantadine hydrochloride, 100 mg, was given twice daily for 13 days to 12 healthy volunteers. On day 11, aspirin (650 mg, four times daily) was started and continued for 8 days. The pharmacokinetics of rimantadine were assessed on days 11 and 13. Peak plasma concentrations and AUC of rimantadine were reduced approximately 10% in the presence of aspirin.

Cimetidine: When a single 100 mg dose of rimantadine hydrochloride was administered with steady-state cimetidine (300 mg four times a day), there were no statistically significant differences in rimantadine Cmax or AUC between rimantadine hydrochloride alone and rimantadine hydrochloride in the presence of cimetdine.

Live Attenuated Influenza Vaccine (LAIV): The concurrent use of rimantadine hydrochloride with live attenuated intranasal influenza vaccine has not been evaluated. However, because of potential interference between these products, the live attenuated intranasal influenza vaccine should not be administered until 48 hours after cessation of rimantadine hydrochloride and rimantadine hydrochloride should not be administered until two weeks after the administration of live attenuated intranasal influenza vaccine unless medically indicated. The concern about potential interference arises principally from the potential for antiviral drugs to inhibit replication of live vaccine virus.

Carcinogenesis, Mutagenesis, and Impairment of Fertility

Carcinogenesis: Oral administration of rimantadine to rats for 2 years at doses up to 100 mg/kg/d [approximately 11 to 14 times the maximum recommended human dose (MRHD) based on AUC] showed no evidence of increased tumor incidence.

Mutagenesis: No mutagenic effects were seen when rimantadine was evaluated in several standard assays for mutagenicity.

Impairment of Fertility: A reproduction study in male and female rats did not show detectable impairment of fertility at dosages up to 60 mg/kg/day (3 times the MRHD based on mg/m^2).

Pregnancy

Teratogenic Effects: There are no adequate and well-controlled studies in pregnant women. Rimantadine is reported to cross the placenta in mice. Rimantadine has been shown to be embryotoxic in rats when given at a dose of 200 mg/kg/d (11 times the MRHD based on mg/m^2). At this dose the embryotoxic effect consisted of increased fetal resorption in rats; this dose also produced a variety of maternal effects including ataxia, tremors, convulsions and significantly reduced weight gain. No embryotoxicity was observed when rabbits were given doses up to 50 mg/kg/d (approximately 0.1 times the MRHD based on AUC), but evidence of a developmental abnormality in the form of a change in the ratio of fetuses with 12 or 13 ribs were noted. This ratio is normally about 50:50 in a litter but was 80:20 after rimantadine treatment. However, in a repeat embryofetal toxicity study in rabbits at doses up to 50 mg/kg/d (approximately 0.1 times the MRHD based on AUC), this abnormality was not observed.

Nonteratogenic Effects: Rimantadine was administered to pregnant rats in a peri- and postnatal reproduction toxicity study at doses of 30 mg/kg/d, 60 mg/kg/d and 120 mg/kg/d (1.7, 3.4 and 6.8 times the MRHD based on mg/m^2). Maternal toxicity during gestation was noted at the two higher doses of rimantadine, and at the highest dose, 120 mg/kg/day, there was an increase in pup mortality during the first 2 to 4 days postpartum. Decreased fertility of the F1 generation was also noted for the two higher doses.

For these reasons, rimantadine hydrochloride should be used during pregnancy only if the potential benefit justifies the risk to the fetus.

Nursing Mothers

Rimantadine hydrochloride should not be administered to nursing mothers because of the adverse effects noted in offspring of rats treated with rimantadine during the nursing period. Rimantadine is concentrated in rat milk in a dose-related manner: 2 to 3 hours following administration of rimantadine, rat breast milk levels were approximately twice those observed in the serum.

Pediatric Use

In children (1 year to 16 years of age), rimantadine hydrochloride is recommended for the prophylaxis of influenza A. The safety and effectiveness of rimantadine hydrochloride in the treatment of symptomatic influenza infection in children (1 year to 16 years of age) have not been established. Prophylaxis studies with rimantadine hydrochloride have not been performed in children below the age of 1 year.

ADVERSE REACTIONS

In 1,027 patients treated with rimantadine hydrochloride in controlled clinical trials at the recommended dose of 200 mg daily, the most frequently reported adverse events involved the gastrointestinal and nervous systems.

Incidence >1%: Adverse events reported most frequently (1 % to 3%) at the recommended dose in controlled clinical trials are shown in the table below.

 | Rimantadine; (n=1,027) | Control; (n=986)
Nervous System
Insomnia | 2.1% | 0.9%
Dizziness | 1.9% | 1.1%
Headache | 1.4% | 1.3%
Nervousness | 1.3% | 0.6%
Fatigue | 1.0% | 0.9%
Gastrointestinal System
Nausea | 2.8% | 1.6%
Vomiting | 1.7% | 0.6%
Anorexia | 1.6% | 0.8%
Dry mouth | 1.5% | 0.6%
Abdominal Pain | 1.4% | 0.8%
Body as a Whole
Asthenia | 1.4% | 0.5%

Less frequent adverse events (0.3 to 1%) at the recommended dose in controlled clinical trials were: Gastrointestinal System: diarrhea, dyspepsia; Nervous System: impairment of concentration, ataxia, somnolence, agitation, depression; Skin and Appendages: rash; Hearing and Vestibular: tinnitus; Respiratory: dyspnea.

Additional adverse events (less than 0.3%) reported at recommended doses in controlled clinical trials were: Nervous System: gait abnormality, euphoria, hyperkinesia, tremor, hallucination, confusion, convulsions; Respiratory: bronchospasm, cough; Cardiovascular: pallor, palpitation, hypertension, cerebrovascular disorder, cardiac failure, pedal edema, heart block, tachycardia, syncope; Reproduction: non-puerperal lactation; Special Senses: taste loss/change, parosmia.

Rates of adverse events, particularly those involving the gastrointestinal and nervous systems, increased significantly in controlled studies using higher than recommended doses of rimantadine hydrochloride. In most cases, symptoms resolved rapidly with discontinuation of treatment. In addition to the adverse events reported above, the following were also reported at higher than recommended doses: increased lacrimation, increased micturition frequency, fever, rigors, agitation, constipation, diaphoresis, dysphagia, stomatitis, hypesthesia and eye pain.

Adverse Reactions in Trials of Rimantadine and Amantadine: In a six-week prophylaxis study of 436 healthy adults comparing rimantadine with amantadine and placebo, the following adverse reactions were reported with an incidence >1%.

 | Rimantadine 200 mg/day; (n=145) | Placebo; (n=143) | Amantadine 200 mg/day; (n=148)
Nervous System
Insomia | 3.4% | 0.7% | 7.0%
Nervousness | 2.1% | 0.7% | 2.8%
Impaired Concentration | 2.1% | 1.4% | 2.1%
Dizziness | 0.7% | 0.0% | 2.1%
Depression | 0.7% | 0.7% | 3.5%
Total % of subjects with adverse reactions | 6.9% | 4.1% | 14.7%
Total % of subjects withdrawn due to adverse reactions | 6.9% | 3.4% | 14.0%

Geriatric Use

Approximately 200 patients over the age of 65 were evaluated for safety in controlled clinical trials with rimantadine hydrochloride. Geriatric subjects who received either 200 mg or 400 mg of rimantadine daily for 1 to 50 days experienced considerably more central nervous system and gastrointestinal adverse events than comparable geriatric subjects receiving placebo. Central nervous system events including dizziness, headache, anxiety, asthenia, and fatigue, occurred up to two times more often in subjects treated with rimantadine than in those treated with placebo. Gastrointestinal symptoms, particularly nausea, vomiting, and abdominal pain occurred at least twice as frequently in subjects receiving rimantadine than in those receiving placebo. The gastrointestinal symptoms appeared to be dose related. In patients over 65, the recommended dose is 100 mg, daily (see CLINCAL PHARMACOLOGY and DOSAGE AND ADMINISTRATION).

To report SUSPECTED ADVERSE REACTIONS, contact Amneal Pharmaceuticals at 1-877-835-5472 or FDA at 1-800-FDA-1088 or www.fda.gov/medwatch.

OVERDOSAGE

As with any overdose, supportive therapy should be administered as indicated. Overdoses of a related drug, amantadine, have been reported with adverse reactions consisting of agitation, hallucinations, cardiac arrhythmia and death. The administration of intravenous physostigmine (a cholinergic agent) at doses of 1 to 2 mg in adults (Ref. 7) and 0.5 mg in children (Ref. 8) repeated as needed as long as the dose did not exceed 2 mg/hour has been reported anecdotally to be beneficial in patients with central nervous system effects from overdoses of amantadine.

DOSAGE AND ADMINISTRATION

For Prophylaxis in Adults and Children

Adults (17 years and older)

The recommended adult dose of rimantadine hydrochloride is 100 mg twice a day. Study durations ranged from 11 days to 6 weeks in adult and elderly patients. In patients with severe hepatic dysfunction, severe renal impairment (CrCl 5 to 29 mL/min) or renal failure (CrCl ≤ 10 mL/min) and in elderly nursing home patients, a dose reduction to 100 mg daily is recommended. Because of the potential for accumulation of rimantadine metabolites during multiple dosing, patients with hepatic or renal impairment should be monitored for adverse effects.

Children (1 year to 16 years of age)

- Study duration ranged from 5 weeks to 6 weeks in pediatric subjects.
- In children 1 year to 9 years of age, rimantadine hydrochloride should be administered once a day, at a dose of 5 mg/kg but not exceeding 150 mg.
- For children 10 years of age or older, use the adult dose.

(see Directions for Compounding of an Oral Suspension from Rimantadine Hydrochloride Tablets to prepare an oral suspension for administration to children and patients with difficulty swallowing tablets).

Children (Birth to 11 months)

The safety and efficacy of rimantadine hydrochloride for prophylaxis of influenza in pediatric patients younger than 1 year of age have not been established.

For Treatment in Adults

Adults (17 years and older)

The recommended adult dose of rimantadine hydrochloride is 100 mg twice a day for 7 days. In patients with severe hepatic dysfunction, severe renal impairment (CrCl 5 to 29 mL/min) or renal failure (CrCl ≤ 10 mL/min) and elderly nursing home patients, a dose reduction to 100 mg daily is recommended. Because of the potential for accumulation of rimantadine metabolites during multiple dosing, patients with hepatic or renal impairment should be monitored for adverse effects. Rimantadine hydrochloride therapy should be initiated as soon as possible, preferably within 48 hours after onset of signs and symptoms of influenza A infection. Therapy should be continued for approximately seven days from the initial onset of symptoms.

Children (16 years of age and younger)

Rimantadine hydrochloride is not indicated for treatment of influenza in pediatric patients 16 years or younger.

Directions for the Compounding of an Oral Suspension from Rimantadine Hydrochloride Tablets (Final Concentration = 10 mg/mL)^1

These directions are provided for use only during emergency situations, for patients who have difficulty swallowing tablets or where lower doses are needed. The pharmacist may compound a suspension (10 mg/mL) from rimantadine hydrochloride tablets, 100 mg using Ora-Sweet®†. Other vehicles have not been studied.

To make an oral suspension (10 mg/mL) from 100 mg rimantadine hydrochloride tablets, you will need the following:

- 100 mg tablets of rimantadine hydrochloride
- Ora-Sweet® (a vehicle manufactured by Paddock Laboratories)
- a graduated cylinder
- a mortar and pestle
- an Amber Glass or Polyethylene terephthalate plastic (PET) bottle
- a funnel (optional)

Compounding Procedures

A 100 mg tablet of rimantadine hydrochloride is required for each 10 mL of compounded oral suspension to make a concentration of 10 mg/mL.

A compounded oral suspension is stable for 14 days. Therefore, the maximum amount of oral suspension that can be dispensed to a patient should not exceed a 14 day supply.

Step A: Guidance for how to determine the Number of Tablets and Total Volume needed to compound a 10 mg/mL oral suspension for each patient.

1. Verify the prescribed dose is correct.

2. Calculate the mg amount of rimantadine hydrochloride needed for the duration of therapy.

(Daily Dose) × (Number of days) = (mg of rimantadine hydrochloride)

For example, 75 mg/day × 10 days = 750 mg

3. Round up the mg of rimantadine hydrochloride amount to the next 100 mg designation.

For example, Round up 750 mg to 800 mg

4. Calculate the Number of 100 mg tablets that are required for the compounded oral suspension.

(Rounded mg of rimantadine hydrochloride) ÷ (100 mg/tablet) = (Number of tablets)

For example, 800 mg ÷ 100 mg/tablet = 8 tablets

5. Calculate the Total Volume of compounded oral suspension (10 mg/mL) (Rounded mg of rimantadine hydrochloride) ÷ (10 mg/mL) = (Total Volume)

For example, 800 mg ÷ 10 mg/mL = 80 mL

Step B: Once the total Number of Tablets and Volume are determined then follow the procedures below for compounding the oral suspension (10 mg/mL) from rimantadine hydrochloride tablets 100 mg

Verify your calculations before you begin to compound an oral suspension.

A 100 mg tablet of rimantadine hydrochloride is required for each 10 mL of compounded oral suspension to make a concentration of 10 mg/mL.

1. Place the required number of rimantadine hydrochloride 100 mg tablets into a clean mortar of sufficient size to contain the tablets and volume of vehicle, Ora-Sweet® used in Step 3.

2. Grind the tablets and triturate to a fine powder using a pestle. Powder on the sides of the mortar or pestle should be removed using a spatula and incorporated into the trituration throughout the process.

3. Slowly add approximately one-third (1/3) of the total volume of vehicle to the mortar while triturating until a uniform suspension is achieved.

4. Transfer the suspension to an amber glass or a PET plastic bottle. Other types of bottles, such as non-PET plastic or uncolored bottles, have not been evaluated and should not be used. A funnel may be used to eliminate any spillage.

5. Slowly add the second one-third (1/3) of the total volume of vehicle to the mortar, rinse the pestle and mortar by a triturating motion and transfer the contents into the bottle.

6. Repeat the rinsing (Step 5) with the remaining one-third (1/3) of the vehicle, transferring the remaining contents to the fullest extent possible. Verify that the suspension is at the desired total volume or add additional vehicle if needed.

7. Close the bottle using a child-resistant cap.

8. Shake well to ensure homogeneous suspension. (Note: The active drug, rimantadine hydrochloride readily dissolves in the specified vehicle. The suspension is caused by some of the inert ingredients of rimantadine hydrochloride tablets 100 mg which are insoluble in this vehicle.)

Labeling and Dispensing Information for the Compounded Oral Suspension

1. Include an ancillary label on the bottle indicating "Shake Gently Before Use". This compounded suspension should be gently shaken prior to administration to minimize the tendency for air entrapment with the Ora-Sweet® preparation. The need to shake the compounded oral suspension gently prior to administration should be reviewed with the parent or guardian when the suspension is dispensed.

2. Provide an oral dosing device (a graduated oral syringe or spoon) that will measure the prescribed dose (in mL). If possible, mark or highlight the graduation corresponding to the appropriate dose on the oral syringe or spoon for each patient.

3. Include an Expiration Date label according to storage condition (see below) and a "Discard any Unused Portion" label to the bottle. Instruct the parent or guardian that any remaining material following completion of therapy or after the expiration date on the label must be discarded.

STORAGE OF THE PHARMACY-COMPOUNDED SUSPENSION

Room Temperature: Stable for 14 days when stored in ambient room temperature conditions. Other storage conditions have not been studied.

Note: The storage conditions are based on stability studies of compounded oral suspensions, using the above mentioned vehicle, which was placed in amber glass and PET plastic bottles at 25°C (77°F). Stability studies have not been conducted with other vehicles or bottle types.

HOW SUPPLIED

Rimantadine Hydrochloride Tablets USP, 100 mg — Each orange, oval, film-coated, convex-faced tablet is debossed with "G" on one side and "1911" on the other side.

They are available as follows:

Bottles of 100: NDC 0115-1911-01

Bottles of 500: NDC 0115-1911-02

Store at 20° to 25°C (68° to 77°F) [see USP Controlled Room Temperature].

REFERENCES

1. Belshe RB, Burk B, Newman F, et al. J Infect Dis. 1989; 159(3):430-435.

2. Sim IS, Cerruti RL, Connell EV. J Respir Dis. 1989 (Suppl): S46-S51.

3. Hayden FG, Belshe RB, Clover RD, et al. N Engl J Med. 1989; 321(25), 1696-1702.

4. Hall CB, Dolin R, Gala CL, et al. Pediatrics. 1987; 80(2): 275-282.

5. Thompson J, Fleet W, Lawrence E, et al. J Med Virol. 1987; 21(3): 249-255.

6. Belshe RB, Smith MH, Hall CB, et al. J Virol. 1988; 62(5): 1508-1512.

7. Casey DE. N Engl J Med. 1978; 298(9):516.

8. Berkowitz CD. J Pediatr. 1979; 95(1): 144-145.

9. Hayden FG, Sperber SJ, Belshe RB, et al. Antimicrob Agents Chemother. 1991; 35(9): 1741-1747.

10. Deyde VM, Xu X, Bright RA, et al. J Infect Dis. 2007; 196(2): 249-257.

11. CDC. MMWR Morb Mortal Wkly Rep. 2009; 58(16): 433-435.

†Ora-Sweet® is a registered trademark of Paddock Laboratories.

Manufactured by:

Amneal Pharmaceuticals Pvt. Ltd.

Ahmedabad 382220, INDIA

Distributed by:

Amneal Pharmaceuticals LLC

Bridgewater, NJ 08807

Rev. 06-2021-00

PRINCIPAL DISPLAY PANEL

NDC 0115-1911-01

Rimantadine Hydrochloride Tablets, USP

100 mg

Rx only

100 Tablets

Amneal Pharmaceuticals LLC